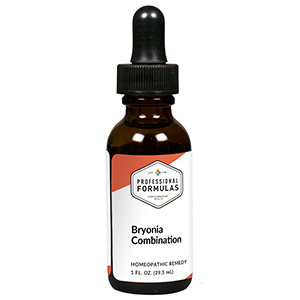 DRUG LABEL: Bryonia Combination
NDC: 63083-9212 | Form: LIQUID
Manufacturer: Professional Complementary Health Formulas
Category: homeopathic | Type: HUMAN OTC DRUG LABEL
Date: 20190815

ACTIVE INGREDIENTS: ACONITUM NAPELLUS WHOLE 4 [hp_X]/29.5 mL; BRYONIA ALBA ROOT 4 [hp_X]/29.5 mL; PHOSPHORUS 5 [hp_X]/29.5 mL; EUPATORIUM PERFOLIATUM FLOWERING TOP 6 [hp_X]/29.5 mL; HAEMOPHILUS INFLUENZAE 12 [hp_X]/29.5 mL; LACHESIS MUTA VENOM 12 [hp_X]/29.5 mL
INACTIVE INGREDIENTS: ALCOHOL; WATER

R212

ACTIVE INGREDIENTS

Aconitum napellus 4X
Bryonia 4X
Phosphorus 5X
Eupatorium perfoliatum 6X
Influenzinum 12X
Lachesis mutus 12X

QUESTIONS

Professional Formulas

PO Box 2034 Lake Oswego, OR 97035

INDICATIONS

For the temporary relief of coughing and irritation, tenderness, or mild pain in the nose or throat.*

PURPOSE

*Claims based on traditional homeopathic practice, not accepted medical evidence. Not FDA evaluated.

WARNINGS

If symptoms do not improve or are accompanied by a fever, consult a doctor. Keep out of the reach of children. In case of overdose, get medical help or contact a poison control center right away. If pregnant or breastfeeding, ask a healthcare professional before use.

Keep out of the reach of children.

PREGNANCY OR BREAST FEEDING

If pregnant or breastfeeding, ask a healthcare professional before use.

DIRECTIONS

Place drops under tongue 30 minutes before/after meals. Adults and children 12 years and over: Take 10 drops up to 3 times per day. Consult a physician for use in children under 12 years of age.

OTHER INFORMATION

Tamper resistant. If seal is broken, do not use. After opening, close container tightly and store at room temperature away from heat.

INACTIVE INGREDIENTS

40% ethanol, purified water.

LABEL

Est 1985

Professional Formulas

Complementary Health

Bryonia Combination

Homeopathic Remedy

1 FL. OZ. (29.5 mL)